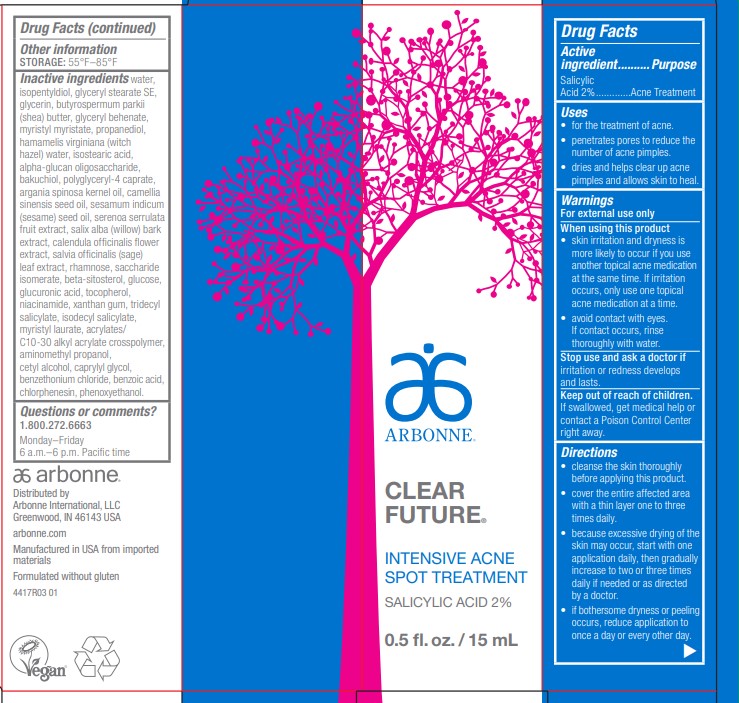 DRUG LABEL: Clear Future Intensive Spot Treatment
NDC: 42508-210 | Form: LOTION
Manufacturer: Arbonne International, LLC
Category: otc | Type: HUMAN OTC DRUG LABEL
Date: 20251203

ACTIVE INGREDIENTS: SALICYLIC ACID 2 mg/15 mL
INACTIVE INGREDIENTS: WATER; ISOPENTYLDIOL; GLYCERYL STEARATE SE; GLYCERIN; SHEA BUTTER; GLYCERYL DIBEHENATE; MYRISTYL MYRISTATE; PROPANEDIOL; HAMAMELIS VIRGINIANA TOP WATER; ISOSTEARIC ACID; .ALPHA.-GLUCAN OLIGOSACCHARIDE; BAKUCHIOL; POLYGLYCERYL-4 CAPRATE; ARGAN OIL; CAMELLIA SINENSIS SEED OIL; SESAME OIL; SAW PALMETTO; SALIX ALBA BARK; CALENDULA OFFICINALIS FLOWER; SAGE; RHAMNOSE; SACCHARIDE ISOMERATE; .BETA.-SITOSTEROL; DEXTROSE, UNSPECIFIED FORM; GLUCURONIC ACID; TOCOPHEROL; NIACINAMIDE; XANTHAN GUM; TRIDECYL SALICYLATE; ISODECYL SALICYLATE; MYRISTYL LAURATE; CARBOMER INTERPOLYMER TYPE A (ALLYL SUCROSE CROSSLINKED); AMINOMETHYLPROPANOL; CETYL ALCOHOL; CAPRYLYL GLYCOL; BENZETHONIUM CHLORIDE; BENZOIC ACID; CHLORPHENESIN; PHENOXYETHANOL

Clear Future®Intensive Spot Treatment

Drug Facts

Active ingredient

Salicylic Acid 2%

Purpose

Acne Treatment

Uses

- for the treatment of acne.
- penetrates pores to reduce the number of acne pimples.
- dries and helps clear up acne pimples and allows skin to heal.

Warnings

For external use only

When using this product

- skin irritation and dryness is more likely to occur if you use another topical acne medication at the same time. If irritation occurs, only use one topical acne medication at a time.
- avoid contact with eyes. If contact occurs, rinse thoroughly with water.

Stop use and ask a doctor if irritation or redness develops and lasts.

Keep out of reach of children. If swallowed, get medical help or contact a Poison Control Center right away.

Directions

- cleanse the skin thoroughly before applying this product.
- cover the entire affected area with a thin layer one to three times daily.
- because excessive drying of the skin may occur, start with one application daily, then gradually increase to two or three times daily if needed or as directed by a doctor.
- if bothersome dryness or peeling occurs, reduce application to once a day or every other day.

Other information

STORAGE: 55°F–85°F

Inactive ingredients

water, isopentyldiol, glyceryl stearate SE, glycerin, butyrospermum parkii (shea) butter, glyceryl behenate, myristyl myristate, propanediol, hamamelis virginiana (witch hazel) water, isostearic acid, alpha-glucan oligosaccharide, bakuchiol, polyglyceryl-4 caprate, argania spinosa kernel oil, camellia sinensis seed oil, sesamum indicum (sesame) seed oil, serenoa serrulata fruit extract, salix alba (willow) bark extract, calendula officinalis flower extract, salvia officinalis (sage) leaf extract, rhamnose, saccharide isomerate, beta-sitosterol, glucose, glucuronic acid, tocopherol, niacinamide, xanthan gum, tridecyl salicylate, isodecyl salicylate, myristyl laurate, acrylates/C10-30 alkyl acrylate crosspolymer, aminomethyl propanol, cetyl alcohol, caprylyl glycol, benzethonium chloride, benzoic acid, chlorphenesin, phenoxyethanol.

Questions or comments?

1.800.272.6663

Monday–Friday
6 a.m.–6 p.m. Pacific time

Distributed by
Arbonne International, LLC
Greenwood, IN 46143 USA

PRINCIPAL DISPLAY PANEL - 15 mL Tube Carton

ARBONNE®

CLEAR
FUTURE®

INTENSIVE ACNE
SPOT TREATMENT

SALICYLIC ACID 2%

0.5 fl. oz. / 15 mL